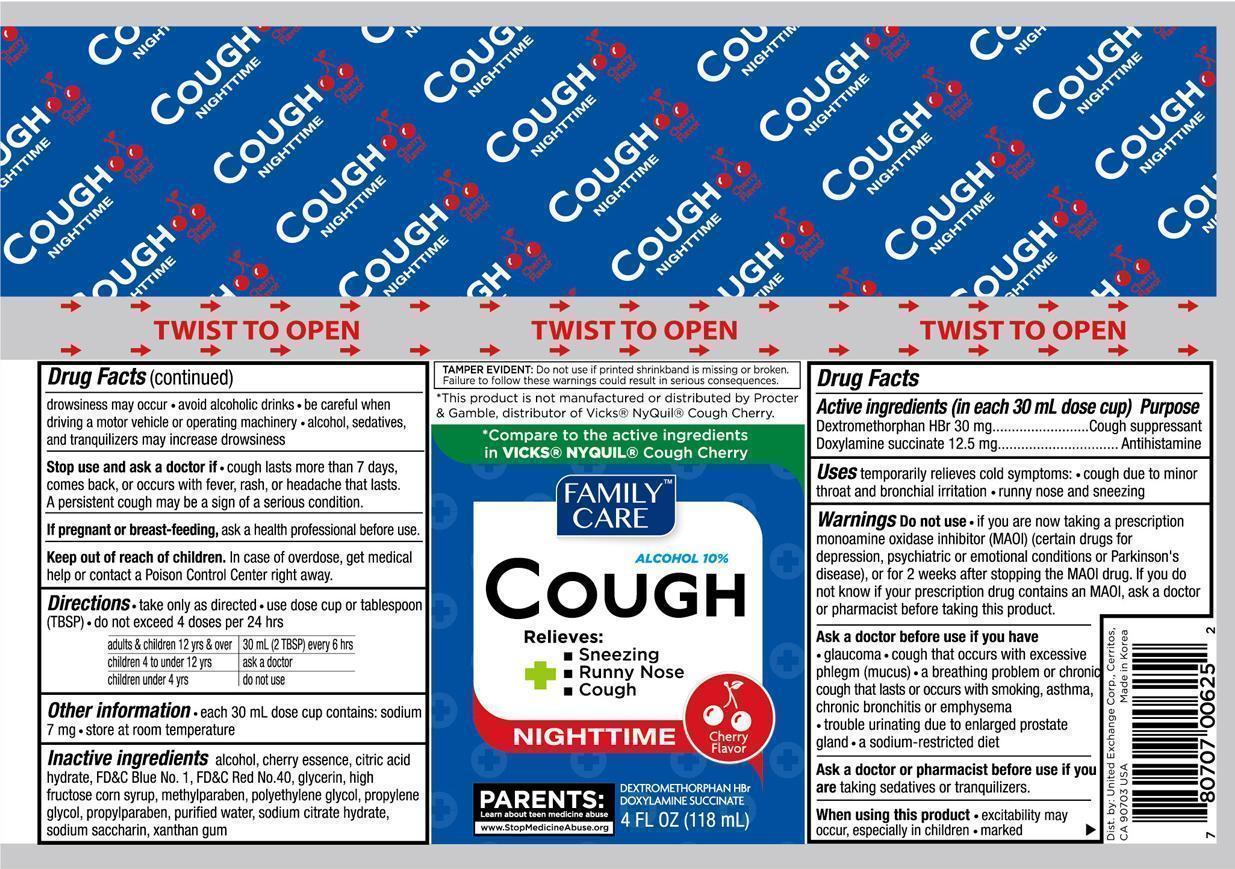 DRUG LABEL: Family Care Cough Nighttime
NDC: 65923-625 | Form: LIQUID
Manufacturer: United Exchange Corp.
Category: otc | Type: HUMAN OTC DRUG LABEL
Date: 20150720

ACTIVE INGREDIENTS: DEXTROMETHORPHAN HYDROBROMIDE 30 mg/30 mL; DOXYLAMINE SUCCINATE 12.5 mg/30 mL
INACTIVE INGREDIENTS: ALCOHOL; CITRIC ACID MONOHYDRATE; FD&C BLUE NO. 1; FD&C RED NO. 40; GLYCERIN; HIGH FRUCTOSE CORN SYRUP; METHYLPARABEN; POLYETHYLENE GLYCOLS; PROPYLENE GLYCOL; PROPYLPARABEN; WATER; SACCHARIN SODIUM; XANTHAN GUM

ACTIVE INGREDIENT

Active ingredients (in each 30 mL dose cup) Purpose

Dextromethorphan HBr 30 mg................................Cough suppressant

Doxylamine succinate 12.5 mg.......................................Antihistamine

PURPOSE

Uses temporarily relieves cold symptoms:

- cough due to minor throat and bronchial irritation
- runny nose and sneezing

Warnings

Do not use

- if you are now taking a prescription monoamine oxidase inhibitor (MAOI) (certain drugs for depression, psychiatric or emotional conditions or Parkinson's disease), or for 2 weeks after stopping the MAOI drug. If you do not know if your prescription drug contains an MAOI, ask a doctor or pharmacist before taking this product.

Ask a doctor before use if you have

- glaucoma
- cough that occurs with excessive phlegm (mucus)
- a breathing problem or chronic cough that lasts or occurs with smoking, asthma, chronic bronchitis or emphysema
- trouble urinating due to enlarged prostate gland
- a sodium-restricted diet

Ask a doctor or pharmacist before use if you are taking sedatives or tranquilizers

When using this product

- excistability may occur, especially in children
- marked drowsiness may occur
- avoid alcoholic drinks
- be careful when driving a motor vehicle or operating machinery
- alcohol, sedatives, and tranquilizers may increase drowsiness

Stop use and ask a doctor if

- cough lasts more than 7 days, comes back, or occurs with fever, rash, or headache that lasts. A persistent cough may be a sign of a serious condition.

PREGNANCY OR BREAST FEEDING

If pregnant or breast-feeding, ask a health professional before use.

Keep out of reach of children. In case of overdose, get medical help or contact a Poison Control Center right away.

Directions

- take only as directed
- use dose cup or tablespoon (TBSP)
- do not exceed 4 doses per 24 hrs

adults & children 12 years over: 30 mL (2 TBSP) every 6 hrs

children 4 to under 12 years: ask a doctor

children under 4 years: do not use

Other information

- each 30 mL dose cup contains: sodium 7 mg
- store at room temperature

Inactive ingredients

alcohol, cherry essence, citric acid hydrate, FD&C Blue No. 1, FD&C Red No. 40, glycerin, high fructose corn syrup, methylparaben, polyethylene glycol, propylene glycol, propylparaben, purified water, sodium citrate hydrate, sodium saccharin, xanthan gum

DOSAGE AND ADMINISTRATION

Distributed by:

United Exchange Corp.

17211 Valley View Ave.

Cerritos, CA 90703

Made in Korea